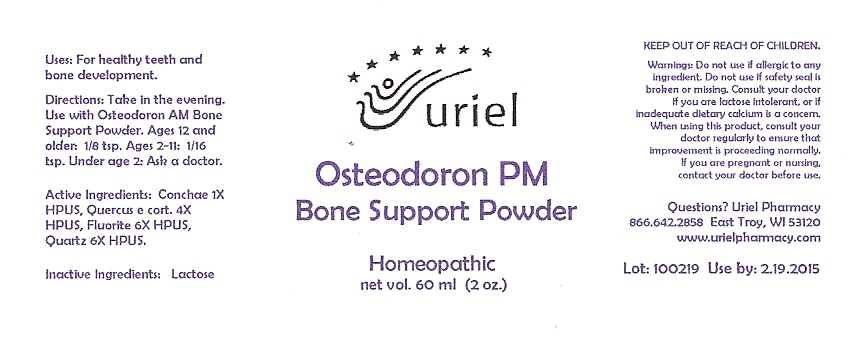 DRUG LABEL: Osteodoron PM Bone Support
NDC: 48951-7097 | Form: POWDER
Manufacturer: Uriel Pharmacy Inc
Category: homeopathic | Type: HUMAN OTC DRUG LABEL
Date: 20100312

ACTIVE INGREDIENTS: OYSTER SHELL CALCIUM CARBONATE, CRUDE 1 [hp_X]/1 1; WHITE OAK BARK 4 [hp_X]/1 1; CALCIUM FLUORIDE 6 [hp_X]/1 1; SILICON DIOXIDE 6 [hp_X]/1 1
INACTIVE INGREDIENTS: LACTOSE

Osteodoron PM Bone Support Powder - 60 ml

Purpose

Uses: For healthy teeth and bone development.

Dosage & Administration

Directions: Take in the evening. Use with Osteodoron AM Bone Support Powder. Ages 12 and older: 1/8 tsp. Ages 2-11: 1/16 tsp. Under age 2: Ask a doctor.

OTC-Active Ingredient

Active Ingredients: Conchae 1X HPUS, Quercus e cort. 4X HPUS, Fluorite 6X HPUS, Quartz 6X HPUS.

Inactive Ingredient

Inactive Ingredient: Lactose

Keep out of reach of children

Do not use section

Warnings:Do not use if allergic to any ingredient. Do not use if safety seal is broken or missing.

Ask doctor section

Consult your doctor if you are lactose intolerant, or if inadequate dietary calcium is a concern. When using this product, consult your doctor regularly to ensure that improvement is proceeding normally.

Pregnancy or breast feeding section

If you are pregnant or nursing, consult a doctor before use.

Questions section

Questions? Uriel Pharmacy
866.642.2858 East Troy, WI 53120
www.urielpharmacy.com

Principal Display Panel

Osteodoron PM

Bone Support Powder

Homeopathic

net vol. 60 ml (2 fl. oz.)